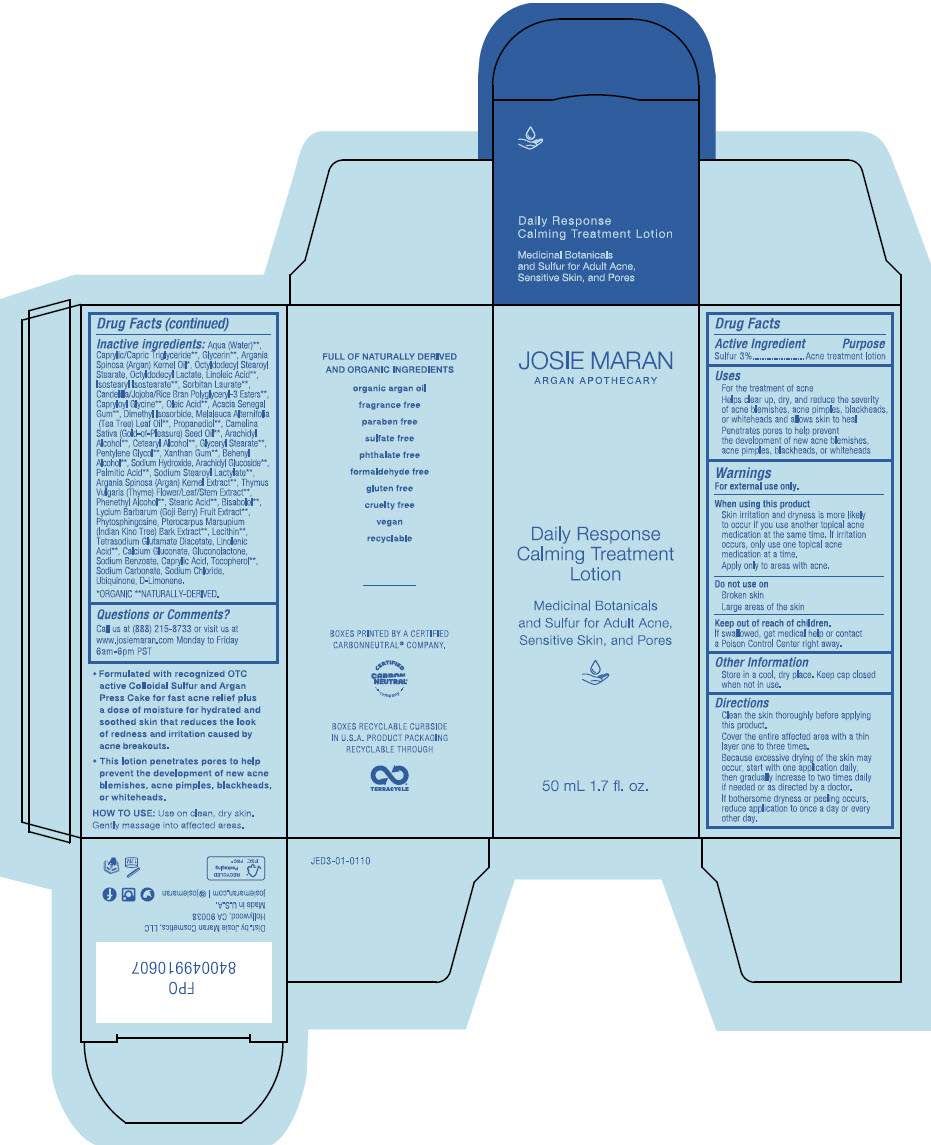 DRUG LABEL: Josie Maran - Argan Apothecary Daily Response Calming Treatment
NDC: 66163-4708 | Form: LOTION
Manufacturer: Cosmetic Solutions LLC
Category: otc | Type: HUMAN OTC DRUG LABEL
Date: 20230313

ACTIVE INGREDIENTS: SULFUR 30 mg/1 mL
INACTIVE INGREDIENTS: Water; MEDIUM-CHAIN TRIGLYCERIDES; GLYCERIN; ARGAN OIL; OCTYLDODECYL STEAROYL STEARATE; LINOLEIC ACID; OCTYLDODECYL LACTATE; ISOSTEARYL ISOSTEARATE; SORBITAN MONOLAURATE; CAPRYLOYL GLYCINE; OLEIC ACID; ACACIA; DIMETHYL ISOSORBIDE; TEA TREE OIL; PROPANEDIOL; CAMELINA SATIVA SEED OIL; ARACHIDYL ALCOHOL; GLYCERYL MONOSTEARATE; PENTYLENE GLYCOL; XANTHAN GUM; DOCOSANOL; SODIUM HYDROXIDE; ARACHIDYL GLUCOSIDE; PALMITIC ACID; SODIUM STEAROYL LACTYLATE; ARGANIA SPINOSA SEED; THYME; PHENYLETHYL ALCOHOL; STEARIC ACID; LEVOMENOL; LYCIUM BARBARUM FRUIT; PHYTOSPHINGOSINE; PTEROCARPUS MARSUPIUM BARK; LECITHIN, SOYBEAN; TETRASODIUM GLUTAMATE DIACETATE; LINOLENIC ACID; CALCIUM GLUCONATE; GLUCONOLACTONE; SODIUM BENZOATE; CAPRYLIC ACID; TOCOPHEROL; SODIUM CARBONATE; SODIUM CHLORIDE; UBIDECARENONE; LIMONENE, (+)-

Josie Maran - Argan Apothecary Daily Response Calming Treatment Lotion

Drug Facts

Active Ingredient

Sulfur 3%

Purpose

Acne treatment lotion

Uses

- For the treatment of acne
- Helps clear up, dry, and reduce the severity of acne blemishes, acne pimples, blackheads, or whiteheads and allows skin to heal
- Penetrates pores to help prevent the development of new acne blemishes, acne pimples, blackheads, or whiteheads

Warnings

For external use only.

When using this product

- Skin irritation and dryness is more likely to occur if you use another topical acne medication at the same time. If irritation occurs, only use one topical acne medication at a time.
- Apply only to areas with acne.

Do not use on

- Broken skin
- Large areas of the skin

Keep out of reach of children.

If swallowed, get medical help or contact a Poison Control Center right away.

Other Information

- Store in a cool, dry place. Keep cap closed when not in use.

Directions

- Clean the skin thoroughly before applying this product.
- Cover the entire affected area with a thin layer one to three times.
- Because excessive drying of the skin may occur, start with one application daily, then gradually increase to two times daily if needed or as directed by a doctor.
- If bothersome dryness or peeling occurs, reduce application to once a day or every other day.

Inactive ingredients

Aqua (Water) [NATURALLY-DERIVED.] , Caprylic/Capric Triglyceride, Glycerin, Argania Spinosa (Argan) Kernel Oil [ORGANIC] , Octyldodecyl Stearoyl Stearate, Octyldodecyl Lactate, Linoleic Acid, lsostearyl lsostearate, Sorbitan Laurate, Candelilla/Jojoba/Rice Bran Polyglyceryl-3 Esters, Capryloyl Glycine, Oleic Acid, Acacia Senegal Gum, Dimethyl lsosorbide, Melaleuca Alternifolia (Tea Tree) Leaf Oil, Propanediol, Camelina Sativa (Gold-of-Pleasure) Seed Oil, Arachidyl Alcohol, Cetearyl Alcohol, Glyceryl Stearate, Pentylene Glycol, Xanthan Gum, Behenyl Alcohol, Sodium Hydroxide, Arachidyl Glucoside, Palmitic Acid, Sodium Stearoyl Lactylate, Argania Spinosa (Argan) Kernel Extract, Thymus Vulgaris (Thyme) Flower/Leaf/Stem Extract, Phenethyl Alcohol, Stearic Acid, Bisabolol, Lycium Barbarum (Goji Berry) Fruit Extract, Phytosphingosine, Pterocarpus Marsupium (Indian Kino Tree) Bark Extract, Lecithin, Tetrasodium Glutamate Diacetate, Linolenic Acid, Calcium Gluconate, Gluconolactone, Sodium Benzoate, Caprylic Acid, Tocopherol, Sodium Carbonate, Sodium Chloride, Ubiquinone, D-Limonene.

Questions or Comments?

Call us at (888) 215-8733 or visit us at www.josiemaran.com Monday to Friday 6am-6pm PST

Dist. by Josie Maran Cosmetics, LLC
Hollywood, CA 90038

PRINCIPAL DISPLAY PANEL - 50 mL Bottle Carton

JOSIE MARAN
ARGAN APOTHECARY

Daily Response
Calming Treatment
Lotion

Medicinal Botanicals
and Sulfur for Adult Acne,
Sensitive Skin, and Pores

50 mL 1.7 fl. oz.